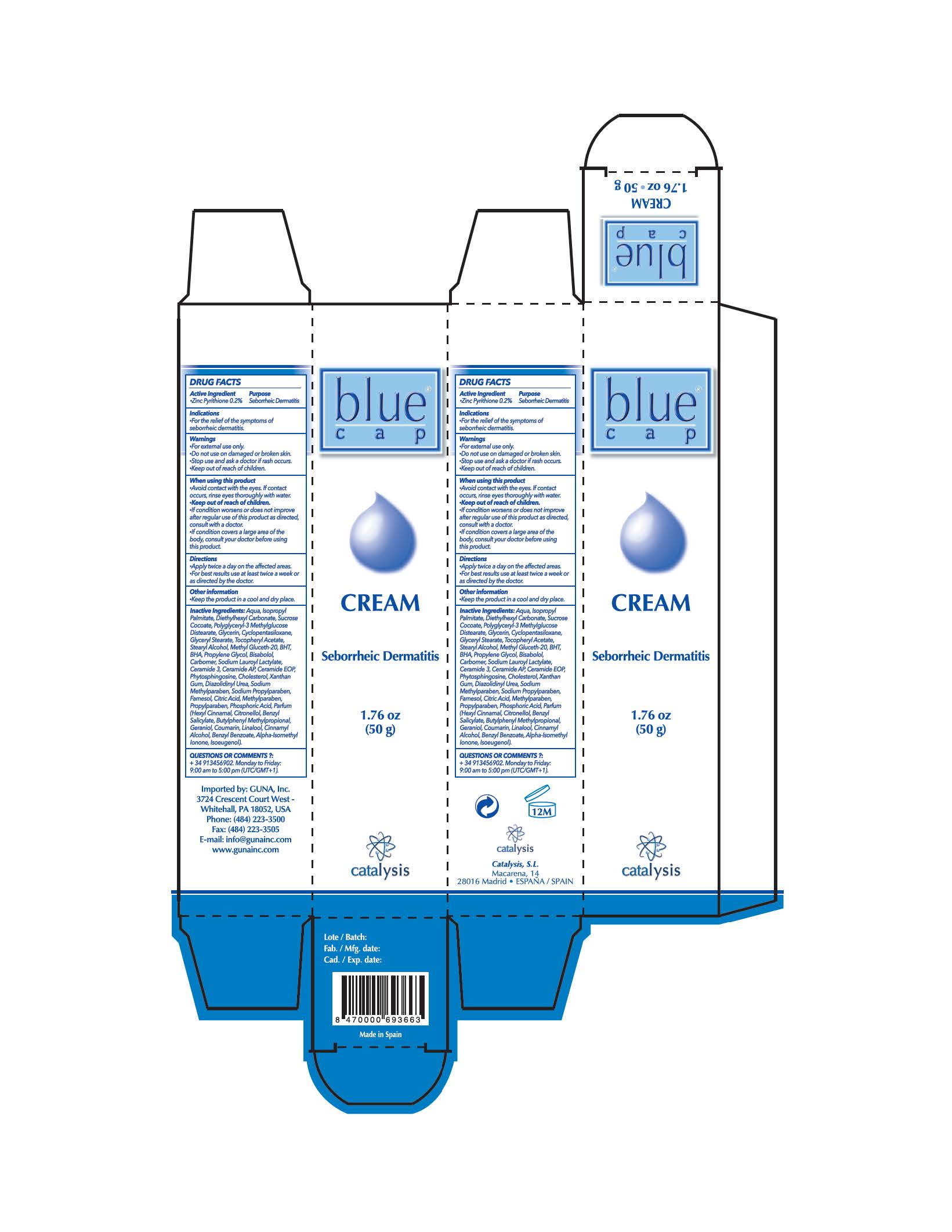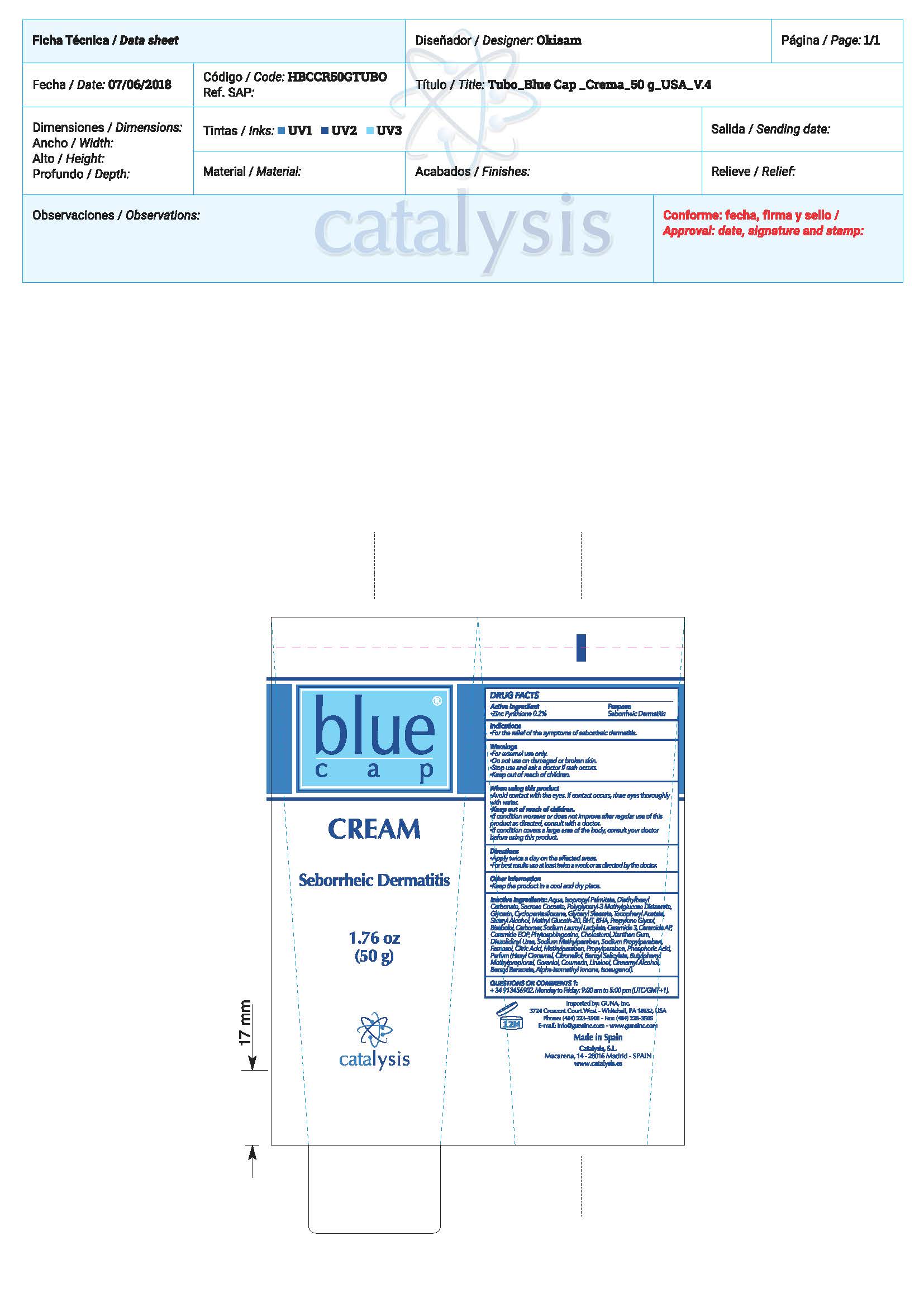 DRUG LABEL: Blue Cap Cream
NDC: 64539-019 | Form: CREAM
Manufacturer: Catalysis, SL
Category: otc | Type: HUMAN OTC DRUG LABEL
Date: 20180729

ACTIVE INGREDIENTS: PYRITHIONE ZINC 0.2 mg/1 mL
INACTIVE INGREDIENTS: DIAZOLIDINYL UREA 0.24 mg/1 mL; CERAMIDE AP 0.01 mg/1 mL; WATER 63.02 mg/1 mL; ISOPROPYL PALMITATE 10 mg/1 mL; DIETHYLHEXYL CARBONATE 9 mg/1 mL; SODIUM LAUROYL LACTYLATE 0.2 mg/1 mL; GLYCERIN 3 mg/1 mL; SUCROSE COCOATE 3.25 mg/1 mL; POLYGLYCERYL-3 DISTEARATE 3.2 mg/1 mL; CYCLOMETHICONE 5 2 mg/1 mL; GLYCERYL MONOSTEARATE 1.4 mg/1 mL; .ALPHA.-TOCOPHEROL ACETATE 0.1 mg/1 mL; STEARYL ALCOHOL 0.6 mg/1 mL; METHYL GLUCETH-20 0.5 mg/1 mL; LINALOOL, (-)- 0.1 mg/1 mL; BUTYLATED HYDROXYTOLUENE 0.5 mg/1 mL; BUTYLATED HYDROXYANISOLE 0.5 mg/1 mL; PROPANEDIOL 0.5 mg/1 mL; GERANIOL 0.1 mg/1 mL; HYDROXYCITRONELLAL 0.1 mg/1 mL; LEVOMENOL 0.445 mg/1 mL; CITRIC ACID MONOHYDRATE 0.05 mg/1 mL; CARBOXYPOLYMETHYLENE 0.206 mg/1 mL; CERAMIDE 3 0.02 mg/1 mL; CERAMIDE 1 0.00002 mg/1 mL; PHYTOSPHINGOSINE 0.01 mg/1 mL; CHOLESTEROL 0.01 mg/1 mL; XANTHAN GUM 0.006 mg/1 mL; METHYLPARABEN SODIUM 0.2 mg/1 mL; PROPYLPARABEN SODIUM 0.1 mg/1 mL; FARNESOL 0.055 mg/1 mL; METHYLPARABEN 0.094 mg/1 mL; PROPYLPARABEN 0.0268 mg/1 mL; PHOSPHORIC ACID 0.0012 mg/1 mL; .BETA.-CITRONELLOL, (S)- 0.1 mg/1 mL; BENZYL SALICYLATE 0.1 mg/1 mL; COUMARIN 0.1 mg/1 mL; BENZYL BENZOATE 0.1 mg/1 mL

Blue Cap Cream

ACTIVE INGREDIENTS PURPOSE

Pyrithione Zinc 0.2%.................. Seborrheic Dermatitis

Warnings

- For external use only.
- Stop use and ask a doctor if rash occurs.
- Do not use on damaged or broken skin
- KEEP out of the reach of children

WARNINGS

- For external use only.
- Stop use and ask a doctor if rash occurs.
- Do not use on damaged or broken skin
- KEEP out of the reach of children

Warnings

Keep out of reach of children

Questions or comments?

+ 34 91 345 6902 M-F 9:00 am to 5:00 pm

Other Information

. keep the product in a cool and dry place

Directions

- apply twice a day on affected area.
- for best results use at least twice a week or as directed by the doctor

DOSAGE AND ADMINISTRATION

- apply twice a day on affected area.
- for best results use at least twice a week or as directed by the doctor

Uses

- For the relief of the symptons of seborrheic dermatitis

Inactive Ingredients

Aqua, Isopropyl Palmitate, Diethylhexyl Carbonate, Sucrose Cocoate, Polyglyceryl-3 Methylglucose Distearate, Glycerin, Cyclopentasiloxane, Glyceryl Stearate. Zinc Pyrithione. Tocopheryl Acetate, Stearyl Alcohol, Methyl Gluceth-20, BHT, BHA, Propylene Glycol, Bisabolol, Carbomer, Sodium Lauroyl Lactylate, Ceramide 3, Ceramide AP, Ceramide EOP, Phytosphingosine, Cholesterol, Xanthan Gum, Diazolidinyl Urea, Sodium Methylparaben, Sodium Propylparaben, Farnesol, Citric Acid, Methylparaben, Propylparaben, Phosphoric Acid, Parfum

Uses

- For the relief of the symptons of seborrheic dermatitis